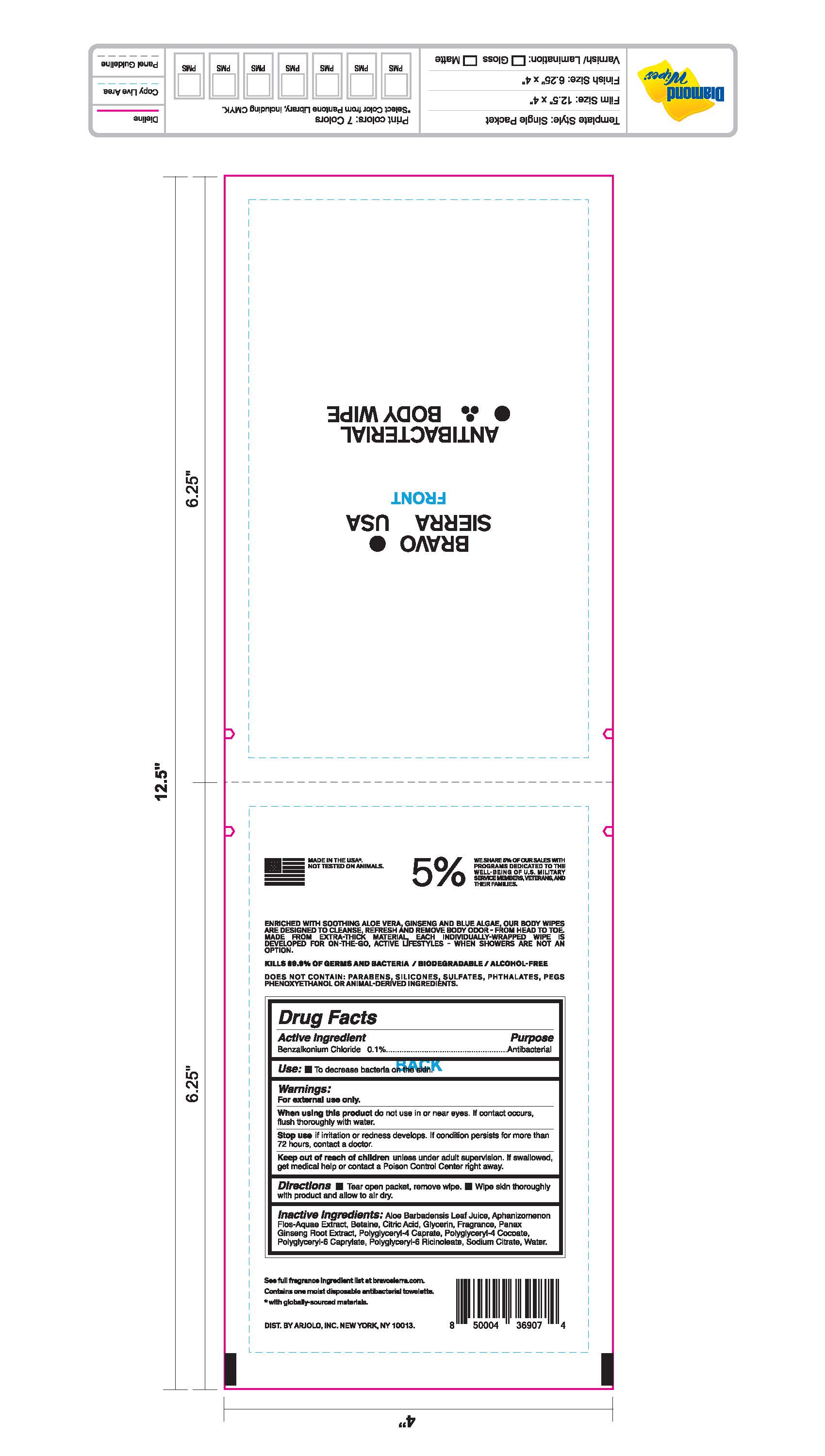 DRUG LABEL: Bravo Sierra USA Face Sunscreen Broad Spectrum SPF 30
NDC: 73206-020 | Form: SWAB
Manufacturer: ARJOLO, INC.
Category: otc | Type: HUMAN OTC DRUG LABEL
Date: 20190716

ACTIVE INGREDIENTS: BENZALKONIUM CHLORIDE 1 g/100 g
INACTIVE INGREDIENTS: ALOE VERA LEAF; APHANIZOMENON FLOSAQUAE; BETAINE; CITRIC ACID MONOHYDRATE; GLYCERIN; PANAX GINSENG WHOLE; POLYGLYCERYL-4 CAPRATE; POLYGLYCERYL-6 ISOSTEARATE; SODIUM CITRATE; WATER

DRUG FACTS

Active Ingredient

Benzalkonium Chloride 0.1%

Purpose

Antibacterial

Use

• To decrease bacteria on the skin.

Warnings

For external use only

When using this product do not use in or near eyes. If contact occurs, flush thoroghly with water.
Stop use if irritation or redness developes. If condition persists for more than 72 hours, contact a doctor.

Keep out of reach of children

unless under adult supervision. If swallowed get medical help or contact a poison control center right away

Directions

• tear open packet, remove wipe.

• wipe skin thorohly with product and allow to air dry.

Inactive ingredients

Aloe Barbadensis Leaf Juice, Aphanimmanon Flos-Aquaa Extract, Betaine, Citric Acud, Glycerin, Fragrance, Panax Ginseng Root Extract, Polyglyceryl-4 Caprate, Polyglyceryl-4 Cocoate, Polyglyceryl-6 Caprylate,Polyglyceryl-6 Ricinoleate, Sodium Citrate, Water.